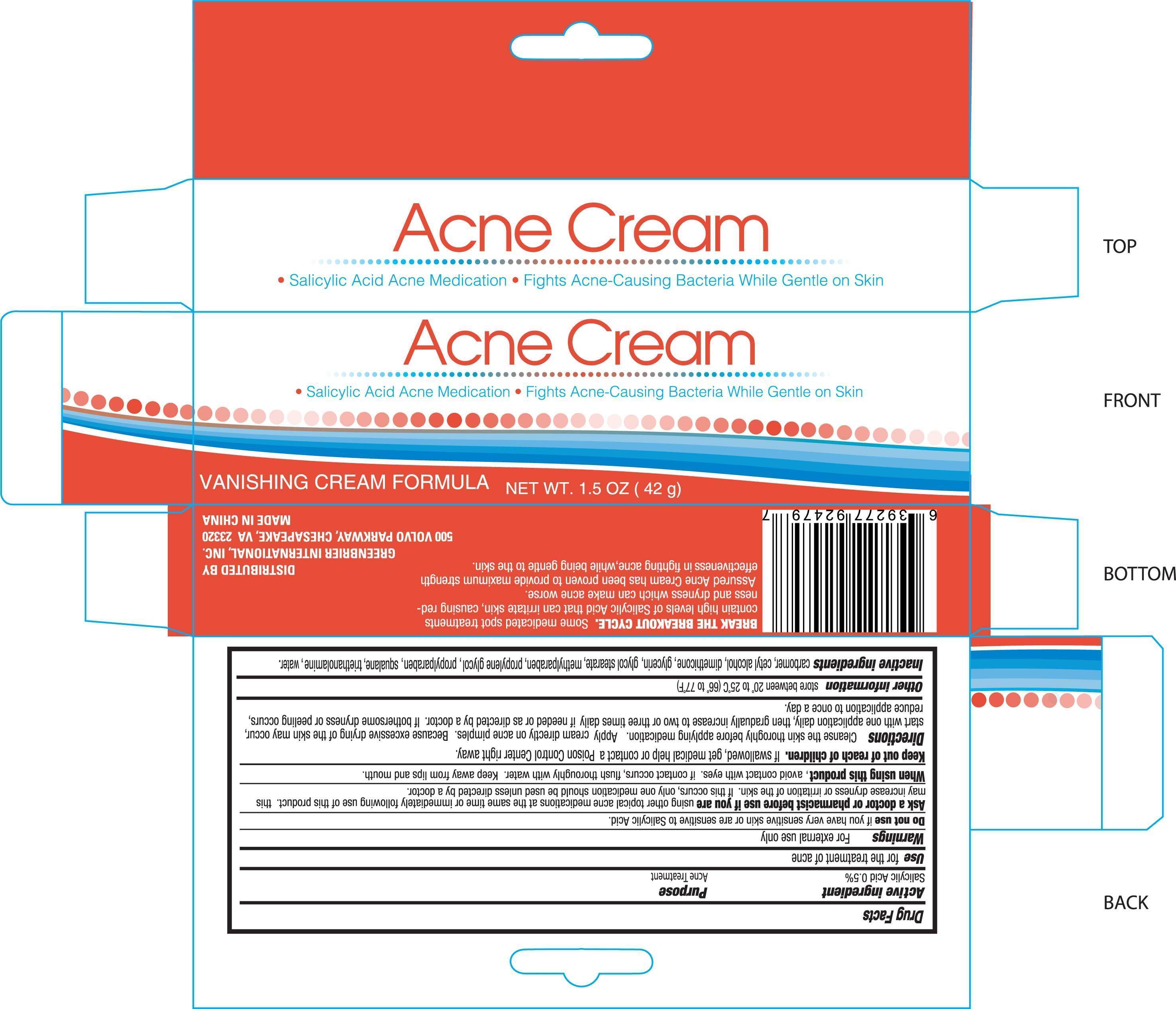 DRUG LABEL: ACNE
NDC: 33992-1307 | Form: CREAM
Manufacturer: GREENBRIER INTERNATIONAL INC
Category: otc | Type: HUMAN OTC DRUG LABEL
Date: 20140721

ACTIVE INGREDIENTS: SALICYLIC ACID 14 g/100 g
INACTIVE INGREDIENTS: DIMETHICONE 2 g/100 g

Active ingredient

Salicylic Acid 0.5%

Purpose

Acne Treatment

Uses

for the treatment of acne

Warnings

For external use only.

Do not use if you have very sensitive skin or are sensitive to Salicylic Acid

Ask a doctor or pharmacist before use if you are using other topical acne medications at the same time or immediately following use of this product. This may increase dryness or irritation of the skin. If this occurs, only one medication should be used unless directed by a doctor.

Keep out of reach of children. If swallowed, get medical help or contact a Poison Control Center right away.

Directions

Cleanse the skin thoroughly before applying medication. Apply cream directly on acne pimples. Because excessive drying of the skin may occur, start with one application daily, then gradually increase to two or three times daily if needed or as directed by a doctor. If bothersome dryness or peeling occurs, reduce application to once a day.

Other information

store at 20 to 25 C (66 to 77 F)

Inactive ingredients

carbomer, cetyl alcohol, dimethicone, glycerin, glycol stearate, methylparaben, propylene glycol, propylparaben, squalane, triethanolamine, water

PACKAGE LABEL

Enter section text here